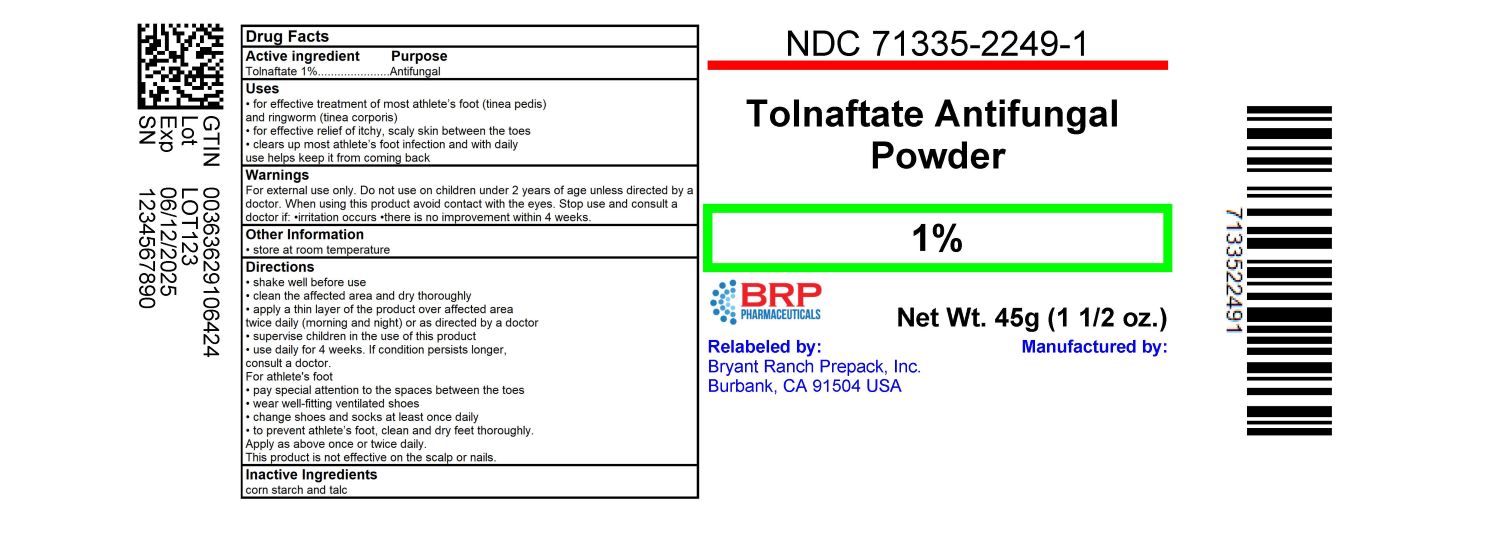 DRUG LABEL: TOLNAFTATE ANTIFUNGAL
NDC: 71335-2249 | Form: POWDER
Manufacturer: Bryant Ranch Prepack
Category: otc | Type: HUMAN OTC DRUG LABEL
Date: 20240129

ACTIVE INGREDIENTS: TOLNAFTATE 1 g/100 g
INACTIVE INGREDIENTS: STARCH, CORN; TALC

GC TOLNAFTATE

Active ingredient

Tolnaftate 1%

PURPOSE

ANTIFUNGAL

USES

• for effective treatment of most athlete’s foot (tinea pedis)

and ringworm (tinea corporis)
• for effective relief of itchy, scaly skin between the toes
• clears up most athlete’s foot infection and with daily
use helps keep it from coming back

WARNINGS

For external use only
Do not use on children under 2 years of age unless
directed by a doctor.
When using this product avoid contact with the eyes
Stop use and consult a doctor if
• irritation occurs
• there is no improvement within 4 weeks

KEEP OUT OF REACH OF CHILDREN

If swallowed, get medical help or contact a Poison Control
Center right away.

DIRECTIONS

• shake well before use

• clean the affected area and dry thoroughly
• apply a thin layer of the product over affected area
twice daily (morning and night) or as directed by a doctor
• supervise children in the use of this product
• use daily for 4 weeks. If condition persists longer,
consult a doctor.

For athlete's foot

• pay special attention to the spaces between the toes
• wear well-fitting ventilated shoes
• change shoes and socks at least once daily
• to prevent athlete’s foot, clean and dry feet thoroughly.
Apply as above once or twice daily.
This product is not effective on the scalp or nails.

Other Information

• store at room temperature

INACTIVE INGREDIENTS

corn starch and talc

HOW SUPPLIED

NDC: 71335-2249-1: 45 g in a BOTTLE

PACKAGE LABEL

Tolnaftate 1% Powder #45